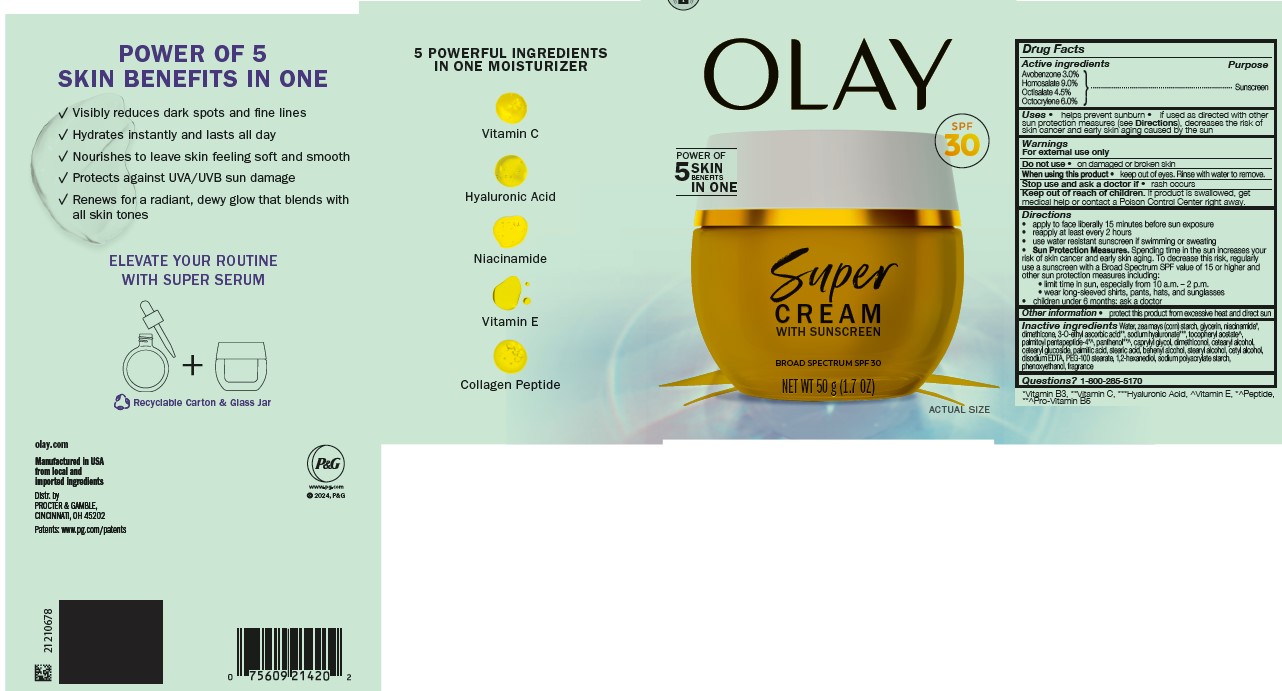 DRUG LABEL: Olay Super Cream with Sunscreen Broad Spectrum SPF 30
NDC: 84126-153 | Form: CREAM
Manufacturer: The Procter & Gamble Manufacturing Company
Category: otc | Type: HUMAN OTC DRUG LABEL
Date: 20250609

ACTIVE INGREDIENTS: OCTOCRYLENE 6 g/100 g; OCTISALATE 4.5 g/100 g; AVOBENZONE 3 g/100 g; HOMOSALATE 9 g/100 g
INACTIVE INGREDIENTS: PALMITIC ACID; WATER; NIACINAMIDE; DIMETHICONE; ZEA MAYS (CORN) STARCH; STEARYL ALCOHOL; PANTHENOL; PALMITOYL PENTAPEPTIDE-4; PEG-100 STEARATE; CETEARYL GLUCOSIDE; CETEARYL ALCOHOL; BEHENYL ALCOHOL; CETYL ALCOHOL; CAPRYLYL GLYCOL; 1,2-HEXANEDIOL; PHENOXYETHANOL; STEARIC ACID; EDETATE DISODIUM; DIMETHICONOL (50000 CST); GLYCERIN; SODIUM HYALURONATE; SODIUM POLYACRYLATE STARCH (12 MICROMETER PARTICLE); 3-O-ETHYL ASCORBIC ACID; ALPHA-TOCOPHEROL ACETATE

Olay Super Cream with Sunscreen Broad Spectrum SPF 30

Drug Facts

ACTIVE INGREDIENT

AVOBENZONE 3.0%

HOMOSALATE 9.0%

OCTISALATE 4.5%

OCTOCRYLENE 6.0%

PURPOSE

Sunscreen

Uses

- helps prevent sunburn
- if used as directed with other sun protection measures (see Directions), decreases the risk of skin cancer and early skin aging caused by the sun

Warnings

For external use only

Do not use

- on damaged or broken skin

When using this product

- keep out of eyes. Rinse with water to remove.

Stop use and ask a doctor if

- rash occurs

Keep out of reach of children. If product is swallowed, get medical help or contact a Poison Control Center right away.

Directions

- apply liberally 15 minutes before sun exposure
- reapply at least every 2 hours
- use water resistant sunscreen if swimming or sweating
- Sun Protection Measures. Spending time in the sun increases your risk of skin cancer and early skin aging. To decrease this risk, regularly use a sunscreen with a Broad Spectrum SPF value of 15 or higher and other sun protection measures including:
  - limit time in sun, especially from 10 a.m. - 2 p.m.
  - wear long-sleeved shirts, pants, hats, and sunglasses
- children under 6 months: ask a doctor

Other information

- protect this product from excessive heat and direct sun

Inactive ingredients

Water, zea mays (corn) starch, glycerin, niacinamide, dimethicone, 3-O-ethyl ascorbic acid, sodium hyaluronate, tocopheryl acetate, palmitoyl pentapeptide-4, panthenol, caprylyl glycol, dimethiconol, cetearyl alcohol, cetearyl glucoside, palmitic acid, stearic acid, behenyl alcohol, stearyl alcohol, cetyl alcohol, disodium EDTA, PEG-100 stearate, 1,2-hexanediol, sodium polyacrylate starch, phenoxyethanol, fragrance

Questions or comments?

Call 1-800-285-5170

Distr. by PROCTER & GAMBLE,
CINCINNATI, OH 45202

PRINCIPAL DISPLAY PANEL - Carton

OLAY

SUPER

CREAM

WITH SUNSCREEN

BROAD SPECTRUM SPF 30

50 g (1.7 OZ)